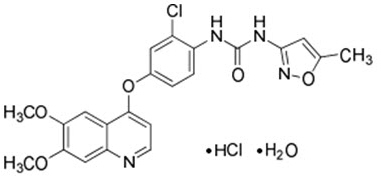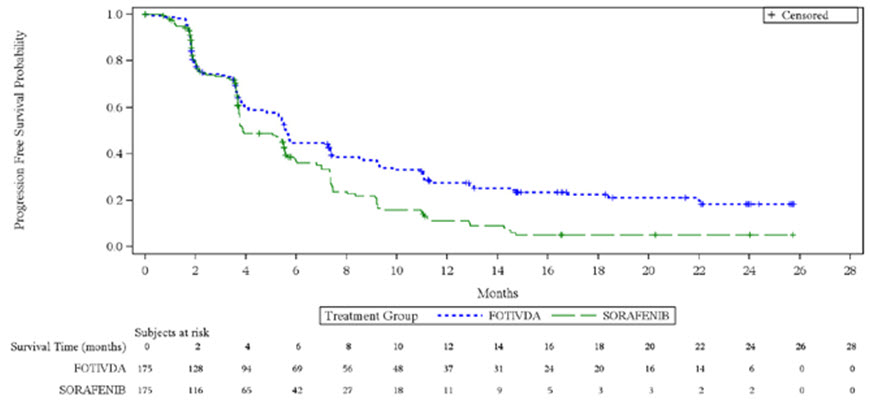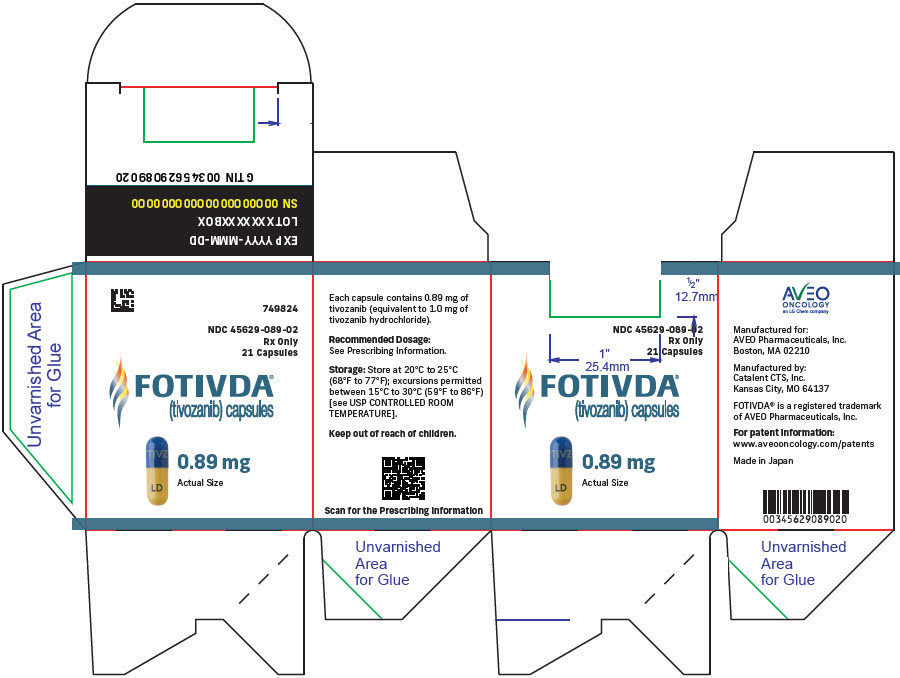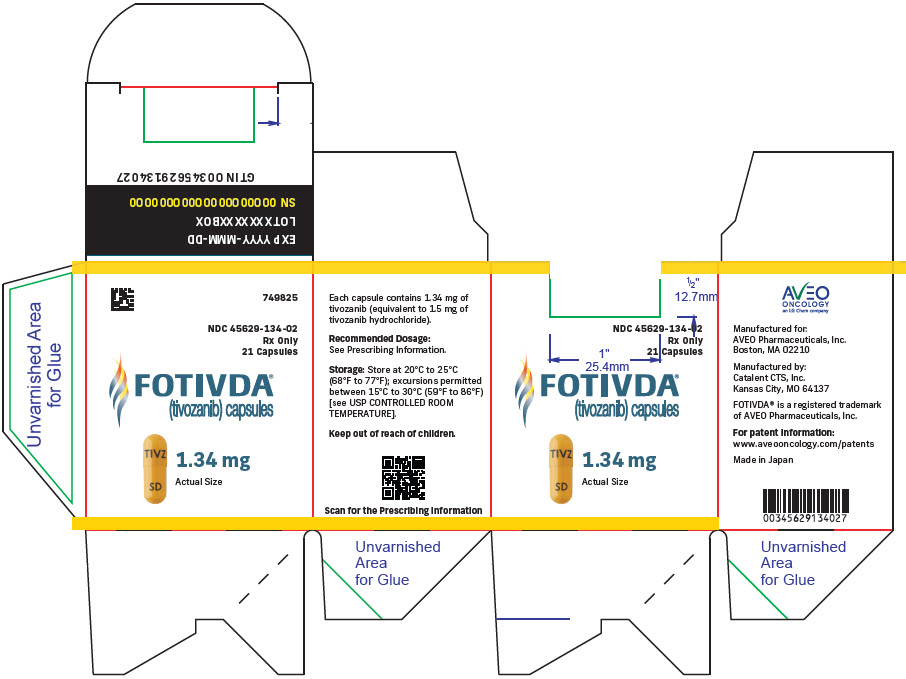 DRUG LABEL: FOTIVDA
NDC: 45629-089 | Form: CAPSULE
Manufacturer: AVEO Pharmaceuticals, Inc.
Category: prescription | Type: HUMAN PRESCRIPTION DRUG LABEL
Date: 20251001

ACTIVE INGREDIENTS: TIVOZANIB HYDROCHLORIDE 0.89 mg/1 1
INACTIVE INGREDIENTS: MANNITOL; MAGNESIUM STEARATE

HIGHLIGHTS OF PRESCRIBING INFORMATION

These highlights do not include all the information needed to use FOTIVDA safely and effectively. See full prescribing information for FOTIVDA.
FOTIVDA®(tivozanib) capsules, for oral use
Initial U.S. Approval: 2021

RECENT MAJOR CHANGES

Warnings and Precautions (5.7) | 8/2024

1 INDICATIONS AND USAGE

FOTIVDA is a kinase inhibitor indicated for the treatment of adult patients with relapsed or refractory advanced renal cell carcinoma (RCC) following two or more prior systemic therapies. (1)

2 DOSAGE AND ADMINISTRATION

- Recommended Dose: 1.34 mg once daily with or without food for 21 days on treatment followed by 7 days off treatment (28-day cycle) until disease progression or unacceptable toxicity. (2.1)
- Dose interruptions and/or dose reduction may be needed to manage adverse reactions. (2.2)
- For patients with moderate hepatic impairment, reduce the dose to 0.89 mg for 21 days on treatment followed by 7 days off treatment (28-day cycle). (2.3)

3 DOSAGE FORMS AND STRENGTHS

Capsules: 1.34 mg and 0.89 mg (3)

4 CONTRAINDICATIONS

None. (4)

5 WARNINGS AND PRECAUTIONS

- Hypertension and Hypertensive Crisis: Control blood pressure prior to initiating FOTIVDA. Monitor for hypertension and treat as needed. For persistent hypertension despite use of anti-hypertensive medications, reduce the FOTIVDA dose. (5.1)
- Cardiac Failure: Monitor for signs or symptoms of cardiac failure throughout treatment with FOTIVDA. (5.2)
- Cardiac Ischemia and Arterial Thromboembolic Events: Closely monitor patients who are at increased risk for these events. Permanently discontinue FOTIVDA for severe arterial thromboembolic events, such as myocardial infarction and stroke. (5.3)
- Venous Thromboembolic Events: Closely monitor patients who are at increased risk for these events. Permanently discontinue FOTIVDA for severe venous thromboembolic events. (5.4)
- Hemorrhagic Events: Closely monitor patients who are at risk for or who have a history of bleeding. (5.5)
- Proteinuria: Monitor throughout treatment with FOTIVDA. For moderate to severe proteinuria, reduce the dose or temporarily interrupt treatment with FOTIVDA. (5.6)
- Perforations and Fistulas: Monitor for symptoms. Discontinue FOTIVDA for severe or life-threatening gastrointestinal perforation. (5.7)
- Thyroid Dysfunction: Monitor before initiation and throughout treatment with FOTIVDA. (5.8)
- Risk of Impaired Wound Healing: Withhold FOTIVDA for at least 24 days before elective surgery. Do not administer for at least 2 weeks following major surgery and adequate wound healing. The safety of resumption of FOTIVDA after resolution of wound healing complications has not been established. (5.9)
- Reversible Posterior Leukoencephalopathy Syndrome (RPLS): Discontinue FOTIVDA if signs or symptoms of RPLS occur. (5.10)
- Embryo-Fetal Toxicity: Can cause fetal harm. Advise patients of the potential risk to a fetus and to use effective contraception. (5.11, 8.1, 8.3)
- Allergic Reactions to Tartrazine: The 0.89 mg capsule of FOTIVDA contains FD&C Yellow No.5 (tartrazine) which may cause allergic-type reactions (including bronchial asthma) in certain susceptible patients. (5.12)

6 ADVERSE REACTIONS

The most common (≥20%) adverse reactions were fatigue, hypertension, diarrhea, decreased appetite, nausea, dysphonia, hypothyroidism, cough, and stomatitis, and the most common Grade 3 or 4 laboratory abnormalities (≥5%) were sodium decreased, lipase increased, and phosphate decreased. (6.1)

To report SUSPECTED ADVERSE REACTIONS, contact AVEO Pharmaceuticals, Inc. at 1-833-FOTIVDA (1-833-368-4832) or FDA at 1-800-FDA-1088 or www.fda.gov/medwatch.

7 DRUG INTERACTIONS

CYP3A Inducers: Avoid concomitant use of strong CYP3A inducers. (7.1)

8 USE IN SPECIFIC POPULATIONS

- Lactation: Advise not to breastfeed. (8.2)
- Females and Males of Reproductive Potential: Can impair fertility. (8.3)
- Hepatic Impairment: Adjust dosage in patients with moderate hepatic impairment. Avoid use in patients with severe hepatic impairment. (2.3, 8.7)

FULL PRESCRIBING INFORMATION

1 INDICATIONS AND USAGE

FOTIVDA is indicated for the treatment of adult patients with relapsed or refractory advanced renal cell carcinoma (RCC) following two or more prior systemic therapies.

2 DOSAGE AND ADMINISTRATION

2.1 Recommended Dosing

The recommended dosage of FOTIVDA is 1.34 mg taken orally once daily for 21 days on treatment followed by 7 days off treatment for a 28-day cycle.

Continue treatment until disease progression or until unacceptable toxicity occurs.

Take FOTIVDA with or without food. Swallow the FOTIVDA capsule whole with a glass of water. Do not open the capsule.

If a dose is missed, the next dose should be taken at the next scheduled time. Do nottake two doses at the same time.

2.2 Dose Modifications for Adverse Reactions

Initiate medical management for diarrhea, nausea, or vomiting prior to dose interruption or reduction.

If dose modifications are required for adverse reactions, reduce the dosage of FOTIVDA to 0.89 mg for 21 days on treatment followed by 7 days off treatment for a 28-day cycle.

Recommendations for dosage modifications are provided in Table 1.

Table 1. Dosage Modifications for Adverse Reactions
Adverse Reaction | Severity [Grades are based on the National Cancer Institute Common Terminology Criteria for Adverse Events (CTCAE).] | Dosage Modifications for FOTIVDA
Hypertension [see Warnings and Precautions (5.1)] | Grade 3 | - Withhold for Grade 3 that persists despite optimal anti-hypertensive therapy. - Resume at reduced dose when hypertension is controlled at less than or equal to Grade 2.
 | Grade 4 | - Permanently discontinue.
Cardiac Failure [see Warnings and Precautions (5.2)] | Grade 3 | - Withhold until improves to Grade 0 to 1 or baseline. - Resume at a reduced dose or discontinue depending on the severity and persistence of adverse reaction.
 | Grade 4 | - Permanently discontinue.
Arterial Thromboembolic Events [see Warnings and Precautions (5.3)] | Any Grade | - Permanently discontinue.
Hemorrhagic Events [see Warnings and Precautions (5.5)] | Grade 3 or 4 | - Permanently discontinue.
Proteinuria [see Warnings and Precautions (5.6)] | 2 grams or greater proteinuria in 24 hours | - Withhold until less than or equal to 2 grams of proteinuria per 24 hours. - Resume at a reduced dose. - Permanently discontinue for nephrotic syndrome.
Reversible Posterior Leukoencephalopathy Syndrome [see Warnings and Precautions (5.10)] | Any Grade | - Permanently discontinue.
Other Adverse Reactions | Persistent or intolerable Grade 2 or 3 adverse reaction Grade 4 laboratory abnormality | - Withhold until improves to Grade 0 to 1 or baseline. - Resume at reduced dose.
 | Grade 4 adverse reaction | - Permanently discontinue.

2.3 Dosage Modifications for Moderate Hepatic Impairment

Reduce the recommended dosage of FOTIVDA to 0.89 mg capsule taken orally once daily for 21 days on treatment followed by 7 days off treatment for a 28-day cycle for patients with moderate hepatic impairment [see USE IN SPECIFIC POPULATIONS (8.7)].

3 DOSAGE FORMS AND STRENGTHS

Capsules:

- 1.34 mg: bright yellow opaque cap imprinted with "TIVZ" in dark blue ink and a bright yellow opaque body imprinted with "SD" in dark blue ink.
- 0.89 mg: dark blue opaque cap imprinted with "TIVZ" in yellow ink and a bright yellow opaque body imprinted with "LD" in dark blue ink.

4 CONTRAINDICATIONS

None.

5 WARNINGS AND PRECAUTIONS

5.1 Hypertension and Hypertensive Crisis

FOTIVDA can cause severe hypertension and hypertensive crisis. Hypertension occurred in 45% of patients treated with FOTIVDA, with 22% of the events ≥ Grade 3. Median time to onset of hypertension was 2 weeks (range: 0 – 192 weeks).

Hypertensive crisis occurred in 0.8% of patients .One patient (0.1%) died due to hypertensive emergency after FOTIVDA overdose [see OVERDOSAGE (10)] .

FOTIVDA has not been studied in patients with systolic blood pressure > 150 mmHg or diastolic blood pressure > 100 mmHg.

Control blood pressure prior to treatment with FOTIVDA. Monitor blood pressure after 2 weeks and at least monthly thereafter during treatment with FOTIVDA. Treat patients with anti- hypertensive therapy when hypertension occurs during treatment with FOTIVDA.

Withhold FOTIVDA for severe hypertension despite optimal anti-hypertensive therapy. For persistent hypertension despite use of anti-hypertensive medications, reduce the FOTIVDA dose [see DOSAGE AND ADMINISTRATION (2.2)] .

Discontinue FOTIVDA if hypertension is severe and persistent despite anti-hypertensive therapy and dose reduction of FOTIVDA, or in patients who experience hypertensive crisis.

If FOTIVDA is interrupted, monitor patients receiving anti-hypertensive medications for hypotension.

5.2 Cardiac Failure

FOTIVDA can cause serious, sometimes fatal, cardiac failure. Cardiac failure in FOTIVDA- treated patients occurred in 1.6%, with 1% of events ≥ Grade 3, and 0.6% events were fatal.

FOTIVDA has not been studied in patients with symptomatic cardiac failure within the preceding 6 months before FOTIVDA treatment initiation.

Periodically monitor patients for symptoms of cardiac failure throughout treatment with FOTIVDA.

Management of cardiac failure events may require interruption, dose reduction, or permanent discontinuation of FOTIVDA therapy [see DOSAGE AND ADMINISTRATION (2.2)] .

5.3 Cardiac Ischemia and Arterial Thromboembolic Events

FOTIVDA can cause serious, sometimes fatal, cardiac ischemia and arterial thromboembolic events. Cardiac ischemia in FOTIVDA-treated patients occurred in 3.2%, with 1.5% of events ≥ Grade 3, and 0.4% events were fatal. Arterial thromboembolic events were reported in 2% of FOTIVDA-treated patients, including death due to ischemic stroke (0.1%).

FOTIVDA has not been studied in patients who had an arterial thrombotic event, myocardial infarction, or unstable angina within the preceding 6 months before FOTIVDA treatment initiation.

Closely monitor patients who are at risk for, or who have a history of these events (such as myocardial infarction and stroke), during treatment with FOTIVDA.

Discontinue FOTIVDA in patients who develop any severe or life-threatening arterial thromboembolic event [see DOSAGE AND ADMINISTRATION (2.2)] .

5.4 Venous Thromboembolic Events

FOTIVDA can cause serious, sometimes fatal, venous thromboembolic events. Venous thromboembolic events occurred in 2.4% of patients treated with FOTIVDA, including death (0.3%).

Closely monitor patients who are at risk for, or who have a history of these events during treatment with FOTIVDA.

Discontinue FOTIVDA in patients who develop any severe or life-threatening venous thromboembolic event [see DOSAGE AND ADMINISTRATION (2.2)] .

5.5 Hemorrhagic Events

FOTIVDA can cause serious, sometimes fatal, hemorrhagic events. Hemorrhagic events occurred in 11% of patients treated with FOTIVDA, including death (0.2%).

FOTIVDA has not been studied in patients with significant bleeding within the preceding 6 months before FOTIVDA treatment initiation.

Closely monitor patients who are at risk for or who have a history of bleeding during treatment with FOTIVDA.

Discontinue FOTIVDA in patients who develop severe or life-threatening hemorrhagic events [see DOSAGE AND ADMINISTRATION (2.2)] .

5.6 Proteinuria

FOTIVDA can cause proteinuria. Proteinuria occurred in 8% of FOTIVDA-treated patients with 2% of events Grade 3. Of the patients who developed proteinuria, 3/81 (3.7%) had acute kidney injury either concurrently or later during treatment.

Monitor patients for proteinuria before initiation of, and periodically throughout, treatment with FOTIVDA.

For patients who develop moderate to severe proteinuria, reduce the dose or interrupt FOTIVDA treatment.

Discontinue FOTIVDA in patients who develop nephrotic syndrome [see DOSAGE AND ADMINISTRATION (2.2)] .

5.7 Gastrointestinal Perforation and Fistula Formation

Gastrointestinal perforation including fatal cases, has been reported in patients receiving FOTIVDA. Monitor for symptoms of gastrointestinal perforation or fistula periodically throughout treatment with FOTIVDA. Permanently discontinue FOTIVDA in patients who develop severe or life-threatening gastrointestinal perforation.

5.8 Thyroid Dysfunction

FOTIVDA can cause thyroid dysfunction. Thyroid dysfunction events in FOTIVDA-treated patients occurred in 11%, with 0.3% Grade 3 or 4 events. Hypothyroidism was reported in 8% of patients and hyperthyroidism was reported in 1% of patients.

Monitor thyroid function before initiation of, and periodically throughout, treatment with FOTIVDA.

Treat hypothyroidism and hyperthyroidism to maintain euthyroid state before and during treatment with FOTIVDA.

5.9 Risk of Impaired Wound Healing

Impaired wound healing can occur in patients who receive drugs that inhibit the vascular endothelial growth factor (VEGF) signaling pathway, such as FOTIVDA. Therefore, FOTIVDA has the potential to adversely affect wound healing.

Withhold FOTIVDA for at least 24 days prior to elective surgery. Do not administer for at least 2 weeks following major surgery and until adequate wound healing. The safety of resumption of FOTIVDA after resolution of wound healing complications has not been established.

5.10 Reversible Posterior Leukoencephalopathy Syndrome

Reversible posterior leukoencephalopathy syndrome (RPLS), a syndrome of subcortical vasogenic edema diagnosed by MRI, can occur with FOTIVDA. Perform an evaluation for RPLS in any patient presenting with seizures, headaches, visual disturbances, confusion, or altered mental function.

Discontinue FOTIVDA in patients who develop RPLS [see DOSAGE AND ADMINISTRATION (2.2)] .

5.11 Embryo-Fetal Toxicity

Based on findings from animal studies and its mechanism of action, FOTIVDA can cause fetal harm when administered to a pregnant woman. In embryo-fetal developmental studies, oral administration of tivozanib to pregnant animals during the period of organogenesis caused maternal toxicity, fetal malformations and embryo-fetal death at doses below the maximum recommended clinical dose on a mg/m^2basis.

Advise pregnant woman of the potential risk to the fetus. Advise females of reproductive potential to use effective contraception during treatment with FOTIVDA and for one month after the last dose. Advise males with female partners of reproductive potential to use effective contraception during treatment with FOTIVDA and for one month after the last dose [see USE IN SPECIFIC POPULATIONS (8.1), (8.3)and CLINICAL PHARMACOLOGY (12.1)].

5.12 Allergic Reactions to Tartrazine (FD&C Yellow No.5)

FOTIVDA 0.89 mg capsule contains FD&C Yellow No.5 (tartrazine) as an imprint ink which may cause allergic-type reactions (including bronchial asthma) in certain susceptible patients. Although the overall incidence of FD&C Yellow No.5 (tartrazine) sensitivity in the general population is low, it is frequently seen in patients who also have aspirin hypersensitivity.

6 ADVERSE REACTIONS

The following clinically significant adverse reactions are also described elsewhere in the labeling:

- Hypertension and Hypertensive Crisis [see WARNINGS AND PRECAUTIONS (5.1)]
- Cardiac Failure [see WARNINGS AND PRECAUTIONS (5.2)]
- Cardiac Ischemia and Arterial Thromboembolic Events [see WARNINGS AND PRECAUTIONS (5.3)]
- Venous Thromboembolic Events [see WARNINGS AND PRECAUTIONS (5.4)]
- Hemorrhagic Events [see WARNINGS AND PRECAUTIONS (5.5)]
- Proteinuria [see WARNINGS AND PRECAUTIONS (5.6)]
- Gastrointestinal Perforation and Fistula Formation [see WARNINGS AND PRECAUTIONS (5.7)]
- Thyroid Dysfunction [see WARNINGS AND PRECAUTIONS (5.8)]
- Risk of Impaired Wound Healing [see WARNINGS AND PRECAUTIONS (5.9)]
- Reversible Posterior Leukoencephalopathy Syndrome (RPLS) [see WARNINGS AND PRECAUTIONS (5.10)]

6.1 Clinical Trial Experience

Because clinical studies are conducted under widely varying conditions, adverse reaction rates observed in clinical studies of a drug cannot be directly compared to rates in the clinical studies of another drug and may not reflect the rates observed in practice.

The pooled safety population described in WARNINGS AND PRECAUTIONS reflects exposure to FOTIVDA administered at 1.34 mg orally once daily with or without food for 21 days on treatment followed by 7 days off treatment for a 28-day cycle in 1008 patients with advanced RCC in TIVO-3 and five other monotherapy studies. Among 1008 patients who received FOTIVDA, 52% were exposed for 6 months or longer and 34% were exposed for greater than one year.

Relapsed or Refractory Advanced RCC Following Two or More Prior Systemic Therapies

The safety of FOTIVDA was evaluated in TIVO-3, a randomized, open-label trial in 350 patients with relapsed or refractory advanced RCC who received 2 or 3 prior systemic treatments [see CLINICAL STUDIES (14)] . Patients were randomized (1:1) to receive FOTIVDA 1.34 mg orally once daily for 21 days on treatment followed by 7 days off treatment for a 28-day cycle, or to receive sorafenib 400 mg orally twice a day continuously until disease progression or unacceptable toxicity. Among patients who received FOTIVDA, 53% were exposed for 6 months or longer and 31% were exposed for greater than one year.

Serious adverse reactions occurred in 45% of patients who received FOTIVDA. Serious adverse reactions in > 2% of patients included bleeding (3.5%), venous thromboembolism (3.5%), arterial thromboembolism (2.9%), acute kidney injury (2.3%), and hepatobiliary disorders (2.3%). Fatal adverse reactions occurred in 8% of patients who received FOTIVDA, including pneumonia (1.7%), hepatobiliary disorders (1.2%), respiratory failure (1.2%), myocardial infarction (0.6%), cerebrovascular accident (0.6%), and subdural hematoma (0.6%).

Permanent discontinuation of FOTIVDA due to an adverse reaction occurred in 21% of patients. Adverse reactions which resulted in permanent discontinuation of FOTIVDA in > 2 patients included hepatobiliary disorders, fatigue, and pneumonia.

Dosage interruptions of FOTIVDA due to an adverse reaction occurred in 48% of patients. Adverse reactions which required dosage interruption in > 5% of patients included fatigue, hypertension, decreased appetite, and nausea.

Dose reductions of FOTIVDA due to an adverse reaction occurred in 24% of patients. Adverse reactions which required dose reductions in > 3% of patients included fatigue, diarrhea, and decreased appetite.

The most common (≥ 20%) adverse reactions were fatigue, hypertension, diarrhea, decreased appetite, nausea, dysphonia, hypothyroidism, cough, and stomatitis, and the most common Grade 3 or 4 laboratory abnormalities (≥ 5%) were sodium decreased, lipase increased, and phosphate decreased.

Table 2summarizes the adverse reactions in TIVO-3.

Table 2. Adverse Reactions (≥ 15%) in Patients Who Received FOTIVDA in TIVO-3
Adverse Reaction | FOTIVDA (n = 173) |  | Sorafenib (n = 170)
Adverse Reaction | All Grades (%) | Grade 3 or 4 (%) | All Grades (%) | Grade 3 or 4 (%)
Any | 99 | 67 | 100 | 72
General
Fatigue [Includes fatigue and asthenia] | 67 | 13 | 48 | 12
Vascular
Hypertension [Includes hypertension, blood pressure increased, hypertensive crisis] | 44 | 24 | 31 | 17
Bleeding [Includes hematuria, epistaxis, hemoptysis, hematoma, rectal hemorrhage, vaginal hemorrhage, contusion, gastrointestinal hemorrhage, hematochezia, intraocular hematoma, melena, metrorrhagia, pulmonary hemorrhage, subdural hematoma, gingival bleeding, hematemesis, hemorrhage intracranial, hemorrhoidal hemorrhage, splinter hemorrhages] | 17 | 3 | 12 | 1
Gastrointestinal
Diarrhea [Includes diarrhea and frequent bowel movements] | 43 | 2 | 54 | 11
Nausea | 30 | 0 | 18 | 4
Stomatitis | 21 | 2 | 23 | 2
Vomiting | 18 | 1 | 17 | 2
Metabolism and nutrition
Decreased appetite | 39 | 5 | 30 | 4
Respiratory, thoracic, and mediastinal
Dysphonia | 27 | 1 | 9 | 0
Cough | 22 | 0 | 15 | 1
Dyspnea | 15 | 3 | 11 | 1
Endocrine
Hypothyroidism [Includes hypothyroidism, blood thyroid stimulating hormone increased, tri-iodothyronine decreased, tri-iodothyronine free decreased] | 24 | 1 | 11 | 0
Musculoskeletal
Back pain | 19 | 2 | 16 | 2
Skin and subcutaneous tissue disorders
Rash [Includes dermatitis, dermatitis acneiform, dermatitis contact, drug eruption, eczema, eczema nummular, erythema, erythema multiforme, photosensitivity reaction, pruritus, psoriasis, rash, rash erythematous, rash generalized, rash macular, rash maculo-papular, rash morbilliform, rash pruritic, seborrheic dermatitis, skin exfoliation, skin irritation, skin lesion, swelling face, toxic skin eruption, urticaria] | 18 | 1 | 52 | 15
Palmar-plantar erythrodysesthesia syndrome | 16 | 1 | 41 | 17
Investigations
Weight decreased | 17 | 3 | 22 | 3

Clinically relevant adverse reactions in < 15% of patients who received FOTIVDA included proteinuria, venous thromboembolism, arterial thromboembolism, hyperthyroidism, hepatobiliary disorders, osteonecrosis, cardiac failure, and delirium.

Table 3summarizes the laboratory abnormalities in TIVO-3.

Table 3. Select Laboratory Abnormalities (≥ 10%) That Worsened from Baseline in Patients with Advanced RCC Who Received FOTIVDA
Laboratory Abnormality | FOTIVDA [The denominator used to calculate the rate varied from 139 to 171 based on the number of patients with a baseline value and at least one post-treatment value.] (n = 173) |  | Sorafenib (n = 170)
Laboratory Abnormality | All Grades (%) | Grade 3 or 4 (%) | All Grades (%) | Grade 3 or 4 (%)
Hematology
Lymphocytes decreased | 25 | 5 | 42 | 6
Hemoglobin increased | 19 | 0 | 8 | 0
Platelets decreased | 19 | 0 | 18 | 1
Hemoglobin decreased | 16 | 1 | 27 | 4
Chemistry
Creatinine increased | 50 | 0 | 37 | 1
Glucose increased | 50 | 3 | 40 | 0
Phosphate decreased | 38 | 5 | 63 | 31
Sodium decreased | 36 | 9 | 30 | 11
Lipase increased | 32 | 9 | 36 | 10
ALT increased | 30 | 4 | 29 | 2
Alkaline phosphatase increased | 30 | 4 | 32 | 2
AST increased | 28 | 1 | 31 | 2
Potassium increased | 26 | 3 | 23 | 0
Magnesium decreased | 26 | 0 | 23 | 1
Amylase increased | 23 | 2 | 28 | 3
Calcium increased | 15 | 2 | 7 | 2
Bilirubin increased | 11 | 3 | 11 | 0
Coagulation
Activated partial thromboplastin time prolonged | 26 | 1 | 18 | 0

6.2 Postmarketing Experience

The following adverse reactions have been identified during post-approval use of FOTIVDA. Because these reactions are reported voluntarily from a population of uncertain size, it is not always possible to reliably estimate their frequency or establish a causal relationship to drug exposure.

- Gastrointestinal disorders: Gastrointestinal perforation and pancreatitis

7 DRUG INTERACTIONS

7.1 Effect of Other Drugs on FOTIVDA

Strong CYP3A Inducers

Concomitant use of FOTIVDA with a strong CYP3A inducer decreases tivozanib exposure [see CLINICAL PHARMACOLOGY (12.3)], which may reduce FOTIVDA anti-tumor activity.

Avoid concomitant use of strong CYP3A inducers with FOTIVDA.

8 USE IN SPECIFIC POPULATIONS

8.1 Pregnancy

Risk Summary

Based on findings in animal studies and its mechanism of action, FOTIVDA can cause fetal harm when administered to a pregnant woman [see CLINICAL PHARMACOLOGY (12.1)] . There are no available data on FOTIVDA use in pregnant woman to inform the drug-associated risk. In embryo-fetal developmental studies, oral administration of tivozanib to pregnant animals during the period of organogenesis caused maternal toxicity, fetal malformations and embryo- fetal death at doses below the maximum recommended clinical dose on a mg/m^2basis [see DATA] . Advise pregnant woman of the potential risk to a fetus.

The estimated background risk of major birth defects and miscarriage for the indicated population is unknown. All pregnancies have a background risk of birth defect, loss, or other adverse outcomes. In the U.S. general population, the estimated background risk of major birth defects and miscarriage in clinically-recognized pregnancies is 2% to 4% and 15% to 20% respectively.

Data

Animal Data

In an embryo-fetal developmental study in pregnant rats, daily oral administration of tivozanib at doses ≥ 0.03 mg/kg/day (0.2 times the maximum recommended clinical dose on a mg/m^2basis) during the period of organogenesis resulted in maternal toxicity, increases in early and late resorptions, and an increase in fetal external malformations (body edema, short/kinked tail), and skeletal developmental delays.

In an embryo-fetal developmental study in pregnant rabbits, daily oral administration of tivozanib at 1 mg/kg/day (14.5 times the maximum recommended clinical dose on a mg/m^2basis) during the period of organogenesis resulted in fetal malformations including ventricular septal defects and major vessel anomalies. No maternal toxicity was reported at doses up to 1 mg/kg/day.

8.2 Lactation

Risk Summary

There are no data on the presence of tivozanib in human milk, or the effects of tivozanib on the breastfed child, or on milk production. Because of the potential for serious adverse reactions in a breastfed child, advise a lactating woman not to breastfeed during treatment with FOTIVDA and for one month after the last dose.

8.3 Females and Males of Reproductive Potential

FOTIVDA can cause fetal harm when administered to a pregnant woman [see USE IN SPECIFIC POPULATIONS (8.1)] .

Pregnancy Testing

Verify pregnancy status of females of reproductive potential prior to starting treatment with FOTIVDA.

Contraception

Females

Advise females of reproductive potential to use effective contraception during treatment with FOTIVDA and for one month after the last dose [see USE IN SPECIFIC POPULATIONS (8.1)] .

Males

Advise males with female partners of reproductive potential to use effective contraception during treatment with FOTIVDA and for one month after the last dose [see NONCLINICAL TOXICOLOGY (13.1)] .

Infertility

Females and Males

Based on findings in animal studies, FOTIVDA can impair fertility in females and males of reproductive potential [see NONCLINICAL TOXICOLOGY (13.1)] .

8.4 Pediatric Use

The safety and effectiveness of FOTIVDA in pediatric patients have not been established.

Animal Data

Juvenile animal studies have not been conducted with tivozanib.

In a 13-week repeat-dose study, oral administration of tivozanib to young and growing cynomolgus monkeys resulted in growth plate hypertrophy, absence of active corpora lutea, and no maturing follicles at doses ≥ 0.3 mg/kg/day (4.4 times the maximum recommended clinical dose on a mg/m^2basis). In a 13-week repeat-dose study in rats, teeth abnormalities (thin, brittle teeth, tooth loss, malocclusions) and growth plate hypertrophy were observed following oral administration of tivozanib at doses ≥ 0.1 mg/kg/day (0.7 times the maximum recommended clinical dose on a mg/m^2basis).

8.5 Geriatric Use

Of the 1008 patients with advanced RCC treated with FOTIVDA, 29% were ≥ 65 years of age and 4% were ≥ 75 of age. No overall differences in safety were observed between patients ≥ 65 versus < 65 years of age.

Of the 175 patients with advanced RCC following two or more prior systemic therapies randomized to FOTIVDA, 44% were ≥ 65 years of age and 9% were ≥ 75 of age. No overall differences in effectiveness were observed between patients ≥ 65 versus < 65 years of age.

8.6 Renal Impairment

No dosage modification is recommended for patients with mild to severe renal impairment (creatinine clearance [CLcr] 15-89 mL/min, estimated by Cockcroft-Gault). The recommended dosage for patients with end-stage renal disease has not been established [see CLINICAL PHARMACOLOGY (12.3)] .

8.7 Hepatic Impairment

Reduce the dosage when administering FOTIVDA in patients with moderate (total bilirubin greater than 1.5 to 3 times ULN with any AST) hepatic impairment [see DOSAGE AND ADMINISTRATION (2.3)] . No dosage modification is recommended for patients with mild (total bilirubin less than or equal to ULN with AST greater than ULN or total bilirubin greater than 1 to 1.5 times ULN with any AST) hepatic impairment. The recommended dosage of FOTIVDA in patients with severe (total bilirubin greater than 3 to 10 times ULN with any AST) hepatic impairment has not been established [see CLINICAL PHARMACOLOGY (12.3)] .

10 OVERDOSAGE

Overdosage with FOTIVDA can cause severe hypertension and hypertensive crisis that may result in death [see WARNINGS AND PRECAUTIONS (5.1)] .

During clinical studies, three patients inadvertently received doses ≥ 2.68 mg (≥ 2 times the recommended dose) of FOTIVDA. One patient who received two daily doses of 8.9 mg of FOTIVDA experienced hypertensive crisis with severe hypertensive retinopathy; a second patient who received three doses of 1.34 mg in one day experienced fatal uncontrolled hypertension; and a third patient who received two doses of 1.34 mg FOTIVDA in one day experienced persistent hypertension lasting over 5 days.

There is no specific treatment or antidote for FOTIVDA overdose.

In cases of suspected overdose, withhold FOTIVDA, closely monitor patients for hypertension and hypertensive crisis and other potential adverse reactions. Immediately manage signs or symptoms of hypertension and provide other supportive care as clinically indicated.

11 DESCRIPTION

Tivozanib is a kinase inhibitor. Tivozanib hydrochloride, the active ingredient, has the chemical name 1-{2-chloro-4-[(6,7-dimethoxyquinolin-4-yl)oxy]phenyl}-3-(5-methylisoxazol-3-yl)urea hydrochloride hydrate. The molecular formula is C22H19ClN4O5∙ HCl ∙ H2O and the molecular weight is 509.34 Daltons. The chemical structure is:

Tivozanib hydrochloride is a white to light brown crystalline powder that is practically insoluble in water (0.09 mg/mL).

FOTIVDA 1.34 mg capsule contains 1.5 mg of tivozanib hydrochloride (equivalent to 1.34 mg tivozanib) with inactive ingredients: mannitol and magnesium stearate. Capsule composition: gelatin, titanium dioxide, FDA yellow iron oxide, and Blue SB-6018 (ink).

FOTIVDA 0.89 mg capsule contains 1.0 mg of tivozanib hydrochloride (equivalent to 0.89 mg tivozanib) with inactive ingredients: mannitol and magnesium stearate. Capsule composition: gelatin, titanium dioxide, FDA yellow iron oxide, FD&C Blue #2, Blue SB-6018 (ink) and Yellow SB-3017 (ink). The Yellow SB-3017 ink contains FD&C Yellow No.5 (tartrazine).

12 CLINICAL PHARMACOLOGY

12.1 Mechanism of Action

Tivozanib is a tyrosine kinase inhibitor. In vitro cellular kinase assays demonstrated that tivozanib inhibits phosphorylation of vascular endothelial growth factor receptor (VEGFR)-1, VEGFR-2 and VEGFR-3 and inhibits other kinases including c-kit and PDGFR β at clinically relevant concentrations. In tumor xenograft models in mice and rats, tivozanib inhibited angiogenesis, vascular permeability, and tumor growth of various tumor cell types including human renal cell carcinoma.

12.2 Pharmacodynamics

Exposure-Response Relationship

Tivozanib exposure-response relationships and the time course of pharmacodynamic response have not been fully characterized.

Cardiac Electrophysiology

At the recommended dose of FOTIVDA, no large mean increases (i.e., 20 msec) in QTc interval were observed.

12.3 Pharmacokinetics

The pharmacokinetics of tivozanib were evaluated in patients with solid tumors administered 1.34 mg once daily unless otherwise specified. Steady-state tivozanib AUC and Cmaxincreased in a dose-proportional manner over the dose range of 0.89 to 1.78 mg once daily (0.67 to 1.3 times the recommended dose).

Steady-state was reached by 14 days and the accumulation ratio after administration of 1.34 mg once daily was approximately 6- to 7- fold. Mean steady-state tivozanib [coefficient of variation (CV%)] Cmaxwas 86.9 (44.7%) ng/mL and AUC0-24hwas 1510 (46.1%) ng*h/mL.

Absorption

The median Tmaxof tivozanib is 10 hours with a range of 3 to 24 hours.

Effect of Food

No clinically significant differences in tivozanib AUC or Cmaxwere observed following administration of a high fat meal (approximately 500-600 fat calories, 250 carbohydrate calories and 150 protein calories) in healthy subjects.

Distribution

The apparent volume of distribution (V/F) of tivozanib is 123 L.

Protein binding of tivozanib is ≥ 99%, primarily to albumin in vitro and is independent of concentration. The mean blood-to-plasma concentration ratios ranged from 0.495 to 0.615 in healthy subjects.

Elimination

The apparent clearance (CL/F) of tivozanib is 0.75 L/h and the half-life is 111 hours.

Metabolism

Tivozanib is metabolized predominantly by CYP3A4. Following oral administration of a single radiolabeled 1.34 mg dose of tivozanib to healthy subjects, unchanged tivozanib constituted 90% of the radioactive drug components in serum.

Excretion

Following oral administration of a single radiolabeled 1.34 mg dose of tivozanib to healthy subjects, 79% of the administered dose was recovered in feces (26% unchanged) and 12% in urine (unchanged tivozanib not detected).

Specific Populations

No clinically significant differences in the pharmacokinetics of tivozanib were observed based on age (18 years to 88 years), sex, race (93% Caucasian, 3% African American, 2% Asian, 2% others), body weight (39 kg to 158 kg), mild to severe renal impairment (CLcr 15-89 mL/min as estimated by Cockcroft-Gault) or mild hepatic impairment (total bilirubin less than or equal to ULN with AST greater than ULN or total bilirubin greater than 1 to 1.5 times ULN with any AST). The effect of end-stage renal disease or severe hepatic impairment on tivozanib pharmacokinetics is unknown [see USE IN SPECIFIC POPULATIONS (8.6)and (8.7)] .

Patients with Hepatic Impairment

Compared to subjects with normal hepatic function, tivozanib AUCtauincreased by 1% in patients with mild (total bilirubin less than or equal to ULN with AST greater than ULN or total bilirubin greater than 1 to 1.5 times ULN with any AST) hepatic impairment. Compared to subjects with normal hepatic function, tivozanib AUCtauincreased by 62% in patients with moderate (total bilirubin greater than 1.5 to 3 times ULN with any AST) hepatic impairment. The effect of severe (total bilirubin greater than 3 to 10 times ULN with any AST) hepatic impairment on tivozanib pharmacokinetics has not been studied [see DOSAGE AND ADMINISTRATION (2.3)and USE IN SPECIFIC POPLATIONS (8.7)].

Drug Interaction Studies

Clinical Studies

Strong CYP3A Inducers: Concomitant use of multiple doses of rifampin (strong CYP3A inducer) did not change tivozanib Cmaxbut decreased tivozanib AUC0-INFby 52%.

Strong CYP3A Inhibitors: No clinically significant differences in the pharmacokinetics of tivozanib were observed when multiple doses of ketoconazole (strong CYP3A inhibitor) was co-administered with tivozanib.

In Vitro Studies

Cytochrome P450 (CYP) Enzymes: Tivozanib does not inhibit CYP1A2, CYP2A6, CYP2B6, CYP2C8, CYP2C9, CYP2C19, CYP2D6 or CYP3A4 at clinically relevant concentrations. Tivozanib does not induce CYP1A, CYP2B6, CYP2C9, CYP2C19, or CYP3A at clinically relevant concentrations.

Uridine Diphosphate (UDP)-glucuronosyl Transferase (UGT) Enzymes: Tivozanib does not inhibit UGT at clinically relevant concentrations.

Transporter Systems: Tivozanib inhibits BCRP but does not inhibit P-gp, OCT1, OATP1B1, OATP1B3, BSEP, OAT1, OAT3, OCT2, MATE1 or MATE2-K at clinically relevant concentrations. Tivozanib is not a substrate for P-gp, MRP2, BCRP, OCT1, OATP1B1, OATP1B3, or BSEP.

13 NONCLINICAL TOXICOLOGY

13.1 Carcinogenesis, Mutagenesis, Impairment of Fertility

Carcinogenicity studies have not been conducted with tivozanib.

Tivozanib was not mutagenic in a bacterial reverse mutation (Ames) assay and was not clastogenic in an in vitro cytogenetic assay in Chinese hamster ovary cells or in an in vivo mouse bone marrow micronucleus assay.

In animal studies assessing mating and fertility parameters, oral doses ≥ 0.03 mg/kg/day (0.2 times the maximum recommended clinical dose on a mg/m^2basis) in rats were associated with increased epididymis and testis weights, and doses ≥ 0.3 mg/kg/day (2 times the maximum recommended clinical dose on a mg/m^2basis) reduced mating and produced infertility. An increase in embryo lethality was noted at doses ≥ 0.1 mg/kg/day (0.7 times the maximum recommended clinical dose on a mg/m^2basis).

14 CLINICAL STUDIES

The efficacy of FOTIVDA was evaluated in TIVO-3 (NCT02627963), a randomized (1:1), open- label, multicenter trial of FOTIVDA versus sorafenib in patients with relapsed or refractory advanced RCC who received 2 or 3 prior systemic treatments including at least one VEGFR kinase inhibitor other than sorafenib or tivozanib. Patients were randomized to receive FOTIVDA 1.34 mg orally once daily for 21 days on treatment followed by 7 days off treatment for a 28-day cycle, or to receive sorafenib 400 mg orally twice a day continuously, until disease progression or unacceptable toxicity. Randomization was stratified by prior therapy [two kinase inhibitors (KIs), a KI plus an immune checkpoint inhibitor, or a KI plus other systemic agents] and by International Metastatic Renal Cell Carcinoma Database Consortium (IMDC) prognostic score. Patients were excluded if they had more than 3 prior treatments or Central Nervous System metastases. The main efficacy outcome measure was progression-free survival (PFS) assessed by a blinded independent radiology review committee. Other efficacy endpoints were objective response rate (ORR) and overall survival (OS).

The median age was 63 years (range: 30 to 90 years), 73% were male, 95% were Caucasian, ECOG performance status was 0 in 48% and 1 in 49% of patients (respectively), and 98% of patients had clear cell or clear cell component histology. Prior therapy included two KIs (45%), a KI plus an immune checkpoint inhibitor (26%), and a KI plus another systemic agent (29%). At the time of study entry, 20% of patients had favorable, 61% intermediate, and 19% poor IMDC prognoses.

Efficacy results are summarized in Table 4and Figure 1.

Table 4. Efficacy Results in TIVO-3 (ITT)
Endpoint | FOTIVDA N= 175 | Sorafenib N= 175
Progression Free Survival (PFS) [Assessed by blinded independent radiology review committee according to RECIST v1.1.]
Events, n (%) | 123 (70) | 123 (70)
Progressive Disease | 103 (59) | 109 (62)
Death | 20 (11) | 14 (8)
Median (95% CI), months | 5.6 (4.8, 7.3) | 3.9 (3.7, 5.6)
HR (95% CI) [Based on the Cox proportional hazards model stratified by IMDC prognostic score and prior therapy.] | 0.73 (0.56, 0.95)
P-value [Based on the log-rank test stratified by IMDC prognostic score and prior therapy.] | 0.016
Overall Survival
Deaths, n (%) | 125 (71) | 126 (72)
Median (95% CI), months | 16.4 (13.4, 21.9) | 19.2 (14.9, 24.2)
HR (95% CI) | 0.97 (0.75, 1.24)
Objective Response Rate % (95% CI) | 18 (12, 24) | 8 (4, 13)
Median duration of response in months (95% CI) | NE (9.8, NE) | 5.7 (5.6, NE)
CI: Confidence interval; HR: Hazard ratio (FOTIVDA/sorafenib); NE: not estimable.

Figure 1. Kaplan-Meier Plot of PFS in TIVO-3

16 HOW SUPPLIED/STORAGE AND HANDLING

How Supplied

FOTIVDA (tivozanib) capsules, for oral use are supplied as follows:

Capsule Strength | Opaque Capsule Color | Capsule Markings | Pack Size | NDC Code
Tivozanib 1.34 mg (equivalent to 1.5 mg tivozanib hydrochloride) | Bright yellow cap and body | "TIVZ" imprinted with dark blue ink on cap; "SD" imprinted with dark blue ink on body | Bottle of 21 | NDC 45629-134-01
Tivozanib 0.89 mg (equivalent to 1.0 mg tivozanib hydrochloride) | Dark blue cap and bright yellow body | "TIVZ" imprinted with yellow ink on cap; "LD" imprinted with dark blue ink on body | Bottle of 21 | NDC 45629-089-01
Tivozanib 1.34 mg (equivalent to 1.5 mg tivozanib hydrochloride) | Bright yellow cap and body | "TIVZ" imprinted with dark blue ink on cap; "SD" imprinted with dark blue ink on body | Bottle of 21 in a Carton | NDC 45629-134-02
Tivozanib 0.89 mg (equivalent to 1.0 mg tivozanib hydrochloride) | Dark blue cap and bright yellow body | "TIVZ" imprinted with yellow ink on cap; "LD" imprinted with dark blue ink on body | Bottle of 21 in a Carton | NDC 45629-089-02

Storage and Handling

Store at 20 °C to 25 °C (68 °F to 77 °F); excursions permitted between 15°C to 30 °C (59°F to 86 °F) [see USP CONTROLLED ROOM TEMPERATURE].

Keep out of reach of children.

17 PATIENT COUNSELING INFORMATION

Advise the patient to read the FDA-approved patient labeling [see PATIENT INFORMATION] .

Hypertension and Hypertensive Crisis

Inform patients that hypertension or hypertensive crisis may occur during FOTIVDA treatment. Advise patients to undergo routine blood pressure monitoring and to contact their healthcare provider if blood pressure is elevated. Advise patients that if they experience signs or symptoms of hypertension to immediately contact their healthcare provider [see WARNINGS AND PRECAUTIONS (5.1)].

Cardiac Failure

Advise patients to immediately contact their healthcare provider if they develop symptoms of cardiac failure [see WARNINGS AND PRECAUTIONS (5.2)].

Cardiac Ischemia and Arterial Thromboembolic Events

Inform patients that arterial thromboembolic events (including fatal outcomes) may occur during FOTIVDA treatment. Advise patients to immediately contact their healthcare provider if new onset of chest discomfort, sudden weakness, or other events suggestive of a thrombotic event occurs [see WARNINGS AND PRECAUTIONS (5.3)].

Venous Thromboembolic Events

Advise patients to immediately contact their healthcare provider if they develop symptoms of dyspnea or localized limb edema [see WARNINGS AND PRECAUTIONS (5.4)].

Hemorrhagic Events

Instruct patients to contact their healthcare provider to seek immediate medical attention for signs or symptoms of unusual bleeding or hemorrhage [see WARNINGS AND PRECAUTIONS (5.5)] .

Perforations and Fistulas

Inform patients that gastrointestinal perforations or fistulas may develop during FOTIVDA treatment. Advise patients to immediately contact their healthcare provider if they experience persistent or severe abdominal pain [see WARNINGS AND PRECAUTIONS (5.7)] .

Risk of Impaired Wound Healing

Inform patients that FOTIVDA may impair wound healing. Advise patients that temporary interruption of FOTIVDA is recommended prior to elective surgery. Advise patients to contact their healthcare provider before any planned surgeries, including dental surgery [see DOSAGE AND ADMINISTRATION (2.1)and WARNINGS AND PRECAUTIONS (5.9)] .

Reversible Posterior Leukoencephalopathy Syndrome

Inform patients that RPLS may occur during FOTIVDA treatment. Advise patients to immediately contact their healthcare provider in the event of seizures, headaches, visual disturbances, confusion or difficulty thinking [see WARNINGS AND PRECAUTIONS (5.10)].

Overdosage

Instruct patients to contact their healthcare provider immediately if they inadvertently take too much FOTIVDA [see OVERDOSAGE (10)] .

Embryo-Fetal Toxicity

Advise females of reproductive potential of the potential risk to a fetus. Advise patients to inform their healthcare provider of a known or suspected pregnancy [see WARNINGS AND PRECAUTIONS (5.10)and USE IN SPECIFIC POPULATIONS (8.1)].

Advise females of reproductive potential to use effective contraception during treatment with FOTIVDA and for one month after the last dose.

Advise male patients with female partners of reproductive potential to use effective contraception during treatment with FOTIVDA and for one month after the last dose [see USE IN SPECIFIC POPULATIONS (8.1)and (8.3)and NONCLINICAL TOXICOLOGY (13.1)].

Lactation

Advise women not to breastfeed during treatment with FOTIVDA and for one month after the last dose [see USE IN SPECIFIC POPULATIONS (8.2)].

Infertility

Advise males and females of reproductive potential that FOTIVDA can impair fertility [see USE IN SPECIFIC POPULATIONS (8.3)] .

Allergic Reactions to Tartrazine (FD&C Yellow No.5)

FOTIVDA 0.89 mg capsule contains FD&C Yellow No.5 (tartrazine) as an imprint ink which may cause allergic-type reactions (including bronchial asthma) in certain susceptible patients. Although the overall incidence of FD&C Yellow No.5 (tartrazine) sensitivity in the general population is low, it is frequently seen in patients who also have aspirin hypersensitivity [see WARNINGS AND PRECAUTIONS (5.12)] .

Other Common Events

Advise patients that other adverse reactions with FOTIVDA treatment may include diarrhea, vomiting, dysphonia (hoarseness of voice), fatigue, asthenia and stomatitis (sores in the mouth), and cough [see ADVERSE REACTIONS (6.1)].

Important Administration Information

Instruct patient if a dose of FOTIVDA is missed, the next dose should be taken at the regularly scheduled time. Do not take two doses in the same day [see DOSAGE AND ADMINISTRATION (2.1)] .

Drug Interactions

Advise patients to inform their healthcare provider of all concomitant medications, vitamins, or dietary and herbal supplements [see DRUG INTERACTIONS (7)].

Manufactured for:
AVEO Pharmaceuticals, Inc., an LG Chem company
Boston, MA 02210

Manufactured by:
Catalent CTS, Inc.
Kansas City, MO 64137

For patent information: www.aveooncology.com/patents

©2024 AVEO Pharmaceuticals, Inc. All rights reserved.

PATIENT INFORMATION
FOTIVDA®(fo-TIV-dah)
(tivozanib)
capsules

What is FOTIVDA?
FOTIVDA is a prescription medicine used to treat adults with advanced kidney cancer (advanced renal cell carcinoma or RCC) that has been treated with 2 or more prior medicines and has come back or did not respond to treatment.
It is not known if FOTIVDA is safe and effective in children.

Before taking FOTIVDA, tell your healthcare provider about all your medical conditions, including if you:

- have high blood pressure.
- have a history of heart failure.
- have a history of blood clots in your veins or arteries (types of blood vessels), including stroke, heart attack, or change in vision.
- have bleeding problems.
- have thyroid problems.
- have liver problems.
- have an unhealed wound.
- plan to have surgery or have had recent surgery, including dental surgery. You should stop taking FOTIVDA at least 24 days before planned surgery. See " What are the possible side effects of FOTIVDA?"
- are allergic to FD&C Yellow No.5 (tartrazine) or aspirin.
- are pregnant or plan to become pregnant. FOTIVDA can harm your unborn baby.
  Females who are able to become pregnant:
  - Your healthcare provider should do a pregnancy test before you start treatment with FOTIVDA.
  - Use effective birth control (contraception) during treatment and for 1 month after your last dose of FOTIVDA. Talk to your healthcare provider about birth control methods that may be right for you during this time.
  - Tell your healthcare provider right away if you become pregnant or think you might be pregnant during treatment with FOTIVDA.
  Males with female partners who are able to become pregnant:
  - Use effective birth control (contraception) during treatment and for 1 month after your last dose of FOTIVDA.
  - If your female partner becomes pregnant during your treatment with FOTIVDA, tell your healthcare provider right away.
- are breastfeeding or plan to breastfeed. It is not known if FOTIVDA passes into your breast milk. Do not breastfeed during treatment and for 1 month after your last dose of FOTIVDA.

Tell your healthcare provider about all the medicines you take, including prescription and over-the-counter medicines, vitamins, and herbal supplements. Taking FOTIVDA with certain other medicines may affect how FOTIVDA works.
Know the medicines you take. Keep a list of them to show your healthcare provider and pharmacist when you get a new medicine.

How should I take FOTIVDA?

- Take FOTIVDA exactly as your healthcare provider tells you to take it.
- Take FOTIVDA 1 time each day for 21 days on treatment, followed by 7 days off treatment. This is 1 cycle of treatment. You will repeat this cycle for as long as your healthcare provider tells you to.
- FOTIVDA can be taken with or without food.
- Swallow the FOTIVDA capsule whole with a glass of water. Do not open the capsule.
- If you miss a dose of FOTIVDA, take your next dose at your next scheduled time. Do nottake 2 doses in the same day.
- If you take too much FOTIVDA, call your healthcare provider or go to the nearest hospital emergency room right away.

What are the possible side effects of FOTIVDA?
FOTIVDA may cause serious side effects, including:

- High blood pressure (hypertension). High blood pressure is common with FOTIVDA and may sometimes be severe.FOTIVDA may also cause a sudden, severe increase in your blood pressure (hypertensive crisis) that can lead to death. Your healthcare provider should check your blood pressure after 2 weeks and at least monthly during treatment with FOTIVDA. Your healthcare provider may prescribe medicine to treat your high blood pressure if you develop blood pressure problems. You should check your blood pressure regularly during treatment with FOTIVDA and tell your healthcare provider if you have increased blood pressure. Tell your healthcare provider right away if you get any of the following signs or symptoms:

- confusion
- headaches

- dizziness
- chest pain

- shortness of breath

- Heart failure.FOTIVDA can cause heart failure which can be serious, and sometimes lead to death. Your healthcare provider should check you for symptoms of heart failure regularly during treatment with FOTIVDA. Call your healthcare provider right away if you get symptoms of heart problems, such as shortness of breath or swelling of your ankles.
- Heart attack and blood clots in your veins or arteries.FOTIVDA can cause blood clots which can be serious, and sometimes lead to death. Tell your healthcare provider or get emergency medical help right away if you get any of the following symptoms:

- new chest pain or pressure
- numbness or weakness on one side of your body
- pain in your arms, back, neck or jaw
- trouble talking

- shortness of breath
- sudden severe headache
- vision changes
- swelling in the arms or legs

- Bleeding problems.FOTIVDA can cause bleeding which can be serious, and sometimes lead to death. Tell your healthcare provider or get medical help right away if you develop any of the following signs or symptoms:

- unusual bleeding from the gums
- red or black stools (looks like tar)
- menstrual bleeding or vaginal bleeding that is heavier than normal
- bruises that happen without a known cause or get larger
- headaches, feeling dizzy or weak

- bleeding that is severe or you cannot control
- coughing up blood or blood clots
- pink or brown urine
- vomiting blood or your vomit looks like "coffee grounds"
- unexpected pain, swelling, or joint pain

- Protein in your urine.Your healthcare provider should check your urine for protein before and during your treatment with FOTIVDA.
- Tear (perforation) in your stomach or intestines or an abnormal connection between two or more body parts (fistula).Get medical help right away if you experience tenderness or pain in your stomach-area (abdomen) that is severe and does not go away.
- Thyroid gland problems.Your healthcare provider should do blood tests to check your thyroid gland function before and during your treatment with FOTIVDA. Your healthcare provider may prescribe medicine if you develop thyroid gland problems.
- Risk of wound healing problems.Wounds may not heal properly during FOTIVDA treatment. Tell your healthcare provider if you plan to have surgery before starting or during treatment with FOTIVDA, including dental surgery.
  - You should stop taking FOTIVDA at least 24 days before planned surgery.
  - Your healthcare provider should tell you when you may start taking FOTIVDA again after surgery.

- Reversible Posterior Leukoencephalopathy Syndrome (RPLS).A condition called reversible posterior leukoencephalopathy syndrome (RPLS) can happen during treatment with FOTIVDA. Tell your healthcare provider right away if you get:

- headaches
- seizures

- confusion
- blindness or change in vision

- difficulty thinking

- Allergic reactions to tartrazine (FD&C Yellow No.5).FOTIVDA 0.89 mg capsules contain a dye called FD&C Yellow No.5 (tartrazine) which may cause allergic-type reactions, including bronchial asthma, in certain people. This allergic reaction is most often seen in people who also have an allergy to aspirin.

The most common side effects of FOTIVDA include:

- tiredness
- diarrhea
- decreased appetite
- nausea
- hoarseness
- low levels of thyroid hormones

- cough
- mouth sores
- decreased levels of salt (sodium) and phosphate in the blood
- increased levels of lipase in the blood (a blood test done to check your pancreas)

Other side effects include vomiting and weakness or lack of energy.
FOTIVDA may cause fertility problems in males and females, which may affect your ability to have a child. Talk to your healthcare provider if this is a concern for you.
Your healthcare provider may change your dose, temporarily stop, or permanently stop treatment with FOTIVDA if you have certain side effects.
These are not all of the possible side effects of FOTIVDA.
Call your doctor for medical advice about side effects. You may report side effects to FDA at 1-800-FDA-1088.

How should I store FOTIVDA?

- Store FOTIVDA at room temperature between 68°F to 77°F (20°C to 25°C).

Keep FOTIVDA and all medicines out of the reach of children.

General information about the safe and effective use of FOTIVDA.
Medicines are sometimes prescribed for purposes other than those listed in a Patient Information leaflet. Do not use FOTIVDA for a condition for which it was not prescribed. Do not give FOTIVDA to other people, even if they have the same symptoms you have. It may harm them. You can ask your healthcare provider or pharmacist for information about FOTIVDA that is written for health professionals.

What are the ingredients in FOTIVDA?
Active ingredient:tivozanib hydrochloride
Inactive ingredients:mannitol and magnesium stearate. The capsule contains gelatin, titanium dioxide, FDA yellow iron oxide, and Blue SB-6018 (ink). The 0.89 mg capsule also contains FD&C Blue #2 and Yellow SB-3017 (ink). The Yellow SB-3017 ink contains FD&C Yellow No.5 (tartrazine).
Manufactured for:
AVEO Pharmaceuticals, Inc., an LG Chem Company
Boston, MA 02210
Manufactured by: Catalent CTS, Inc. Kansas City, MO 64137
For more information go to www.fotivda.com or call 1-833-FOTIVDA (1-833-368-4832).
For patent information: www.aveooncology.com/patents
©2024 AVEO Pharmaceuticals, Inc. All rights reserved.

This Patient Information has been approved by the U.S. Food and Drug Administration.

Issued: 08/2024

PRINCIPAL DISPLAY PANEL - 0.89 mg Capsule Bottle Label

NDC 45629-089-02
Rx Only
21 Capsules

FOTIVDA®
(tivozanib) capsules

0.89 mg

Actual Size

PRINCIPAL DISPLAY PANEL - 1.34 mg Capsule Bottle Label

NDC 45629-134-02
Rx Only
21 Capsules

FOTIVDA®
(tivozanib) capsules

1.34 mg

Actual Size